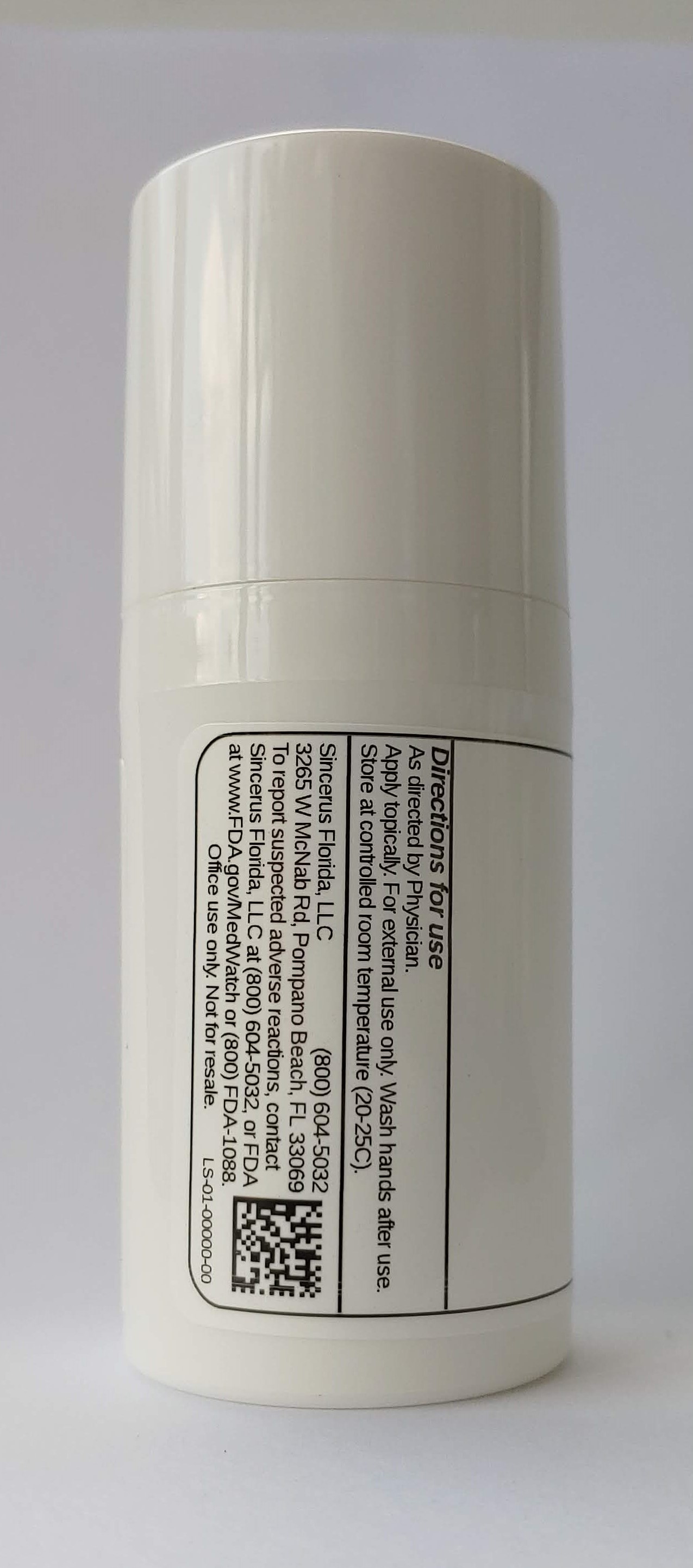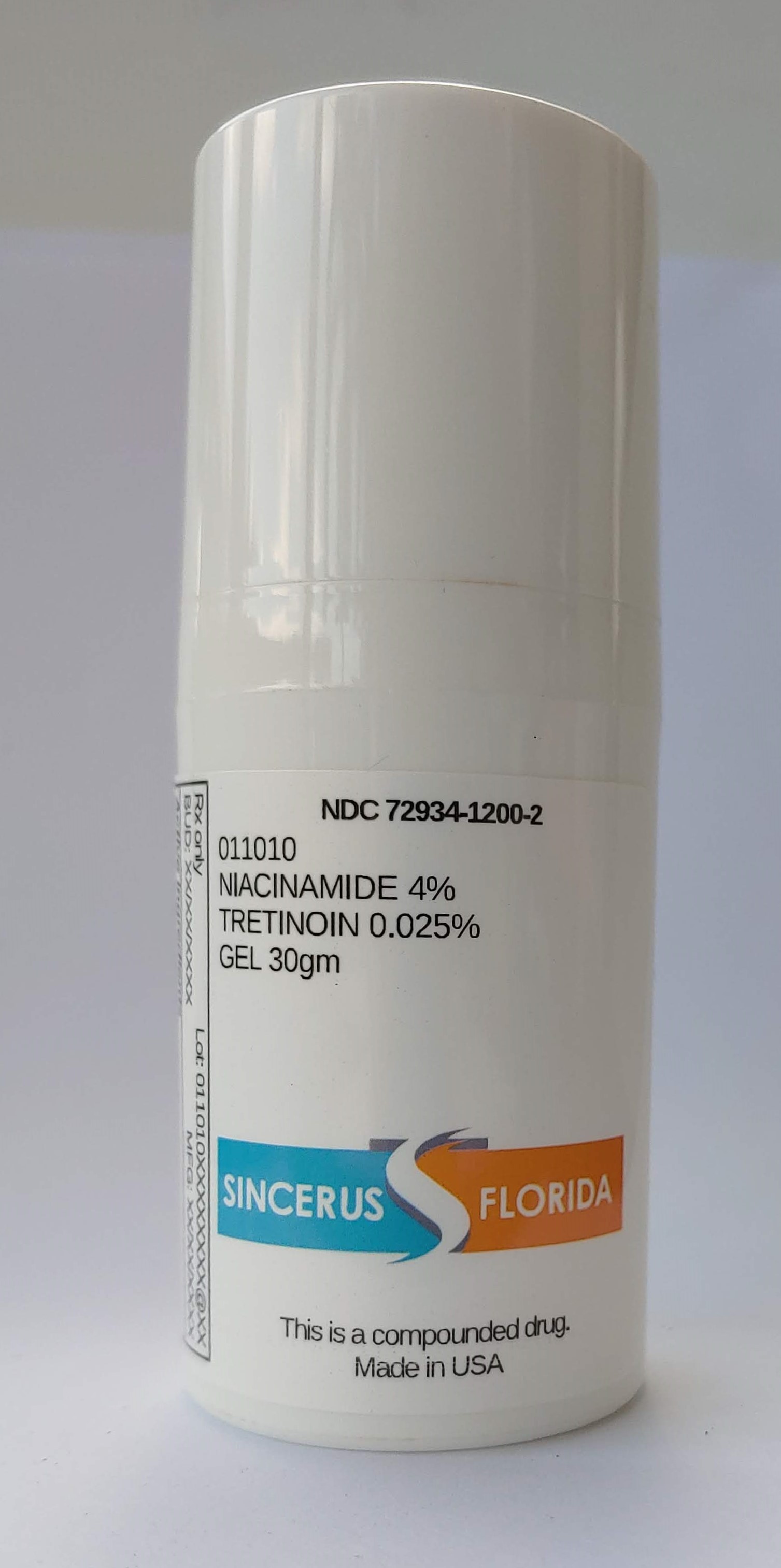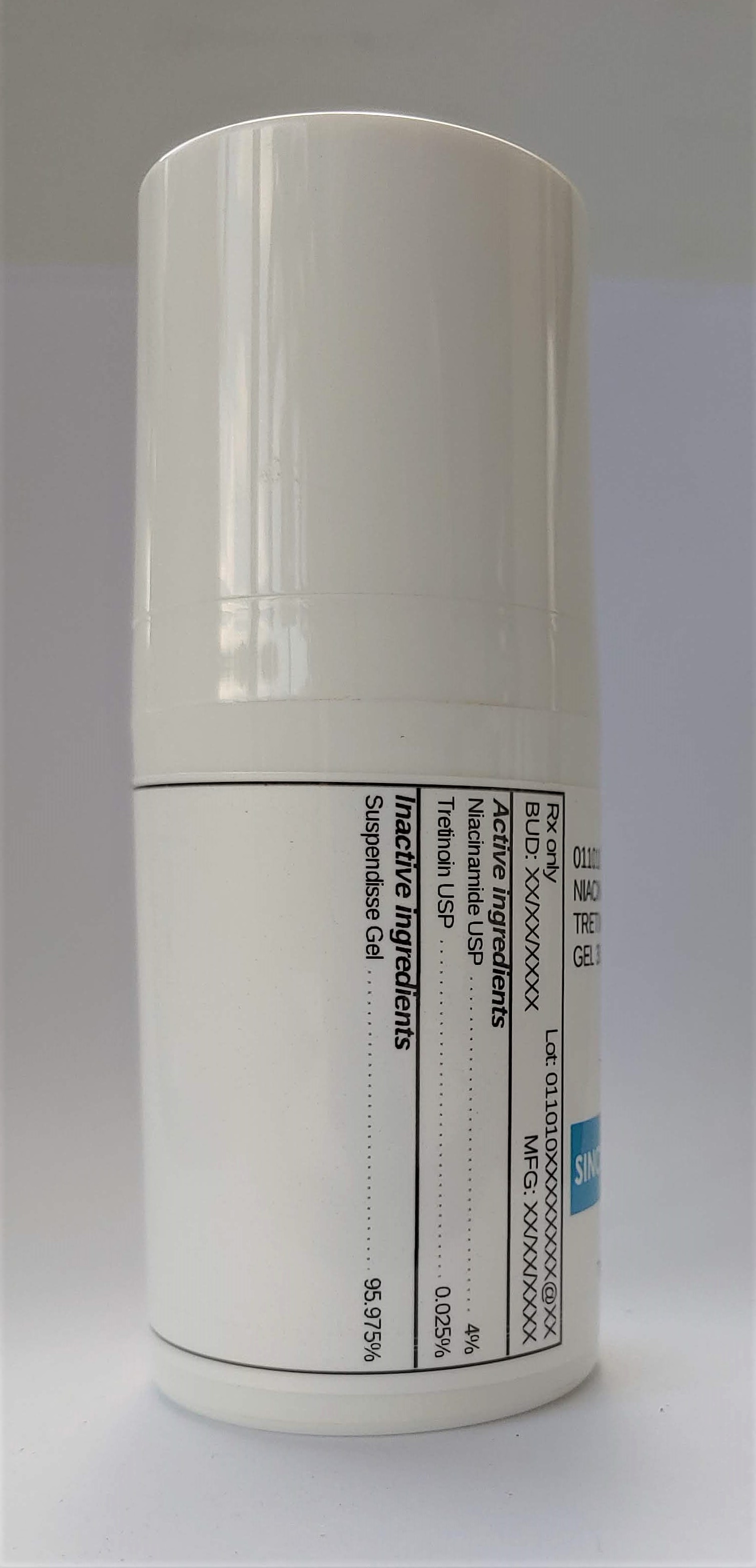 DRUG LABEL: 011010 NIACINAMIDE 4% / TRETINOIN 0.025%
NDC: 72934-1200 | Form: GEL
Manufacturer: Sincerus Florida, LLC
Category: prescription | Type: HUMAN PRESCRIPTION DRUG LABEL
Date: 20200702

ACTIVE INGREDIENTS: TRETINOIN 0.025 g/100 g; NIACINAMIDE 4 g/100 g

011010 NIACINAMIDE 4% / TRETINOIN 0.025%